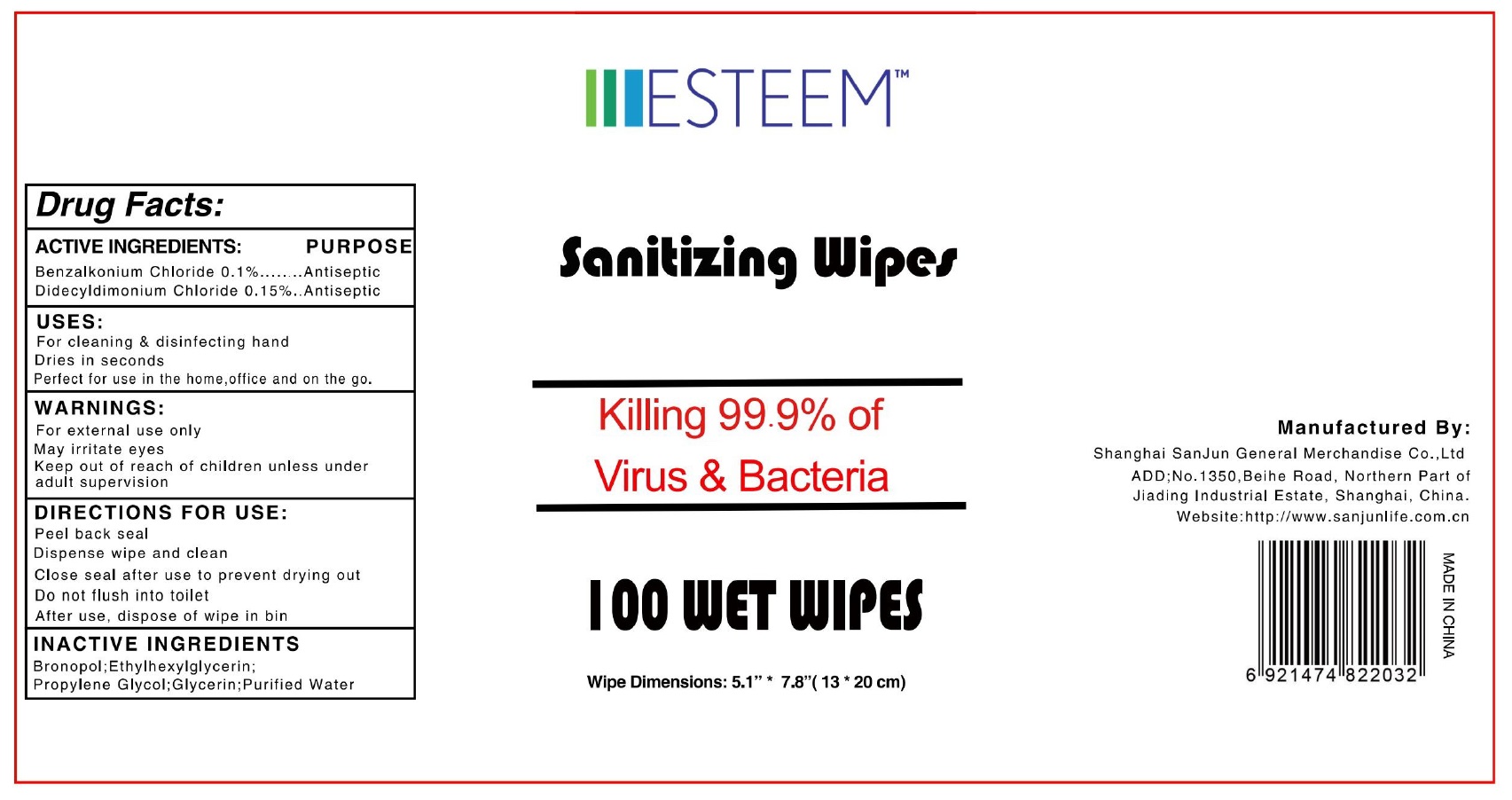 DRUG LABEL: SANITIZING WIPES
NDC: 75670-001 | Form: CLOTH
Manufacturer: SHANGHAI SANJUN GENERAL MERCHANDISE CO., LTD.
Category: otc | Type: HUMAN OTC DRUG LABEL
Date: 20220224

ACTIVE INGREDIENTS: BENZALKONIUM CHLORIDE 0.1 g/100 g; DIDECYLDIMONIUM CHLORIDE 0.15 g/100 g
INACTIVE INGREDIENTS: WATER; BRONOPOL; ETHYLHEXYLGLYCERIN; PROPYLENE GLYCOL; GLYCERIN

75670-001 esteem sanitizing wipes

Active Ingredient

Benzalkonium Chloride 0. 1 %
Didecyldimonium Chloride 0.1 5%

Purpose

Antiseptic
Antiseptic

USE

For cleaning & disinfecting hand
Dries in seconds
Perfect for use in the home,office and on the go.

Warning

For external use only
May irritate eyes

Keep out of reach of children unless under
adult supervision

Directions

Peel back seal
Dispense wipe and clean
Close seal after use to prevent drying out
Do not flush into toilet
After use, dispose of wipe in bin

Inactive ingredients

Bronopol;Ethylhexylglycerin;
Propylene Glycol;Glycerin;Purified Water